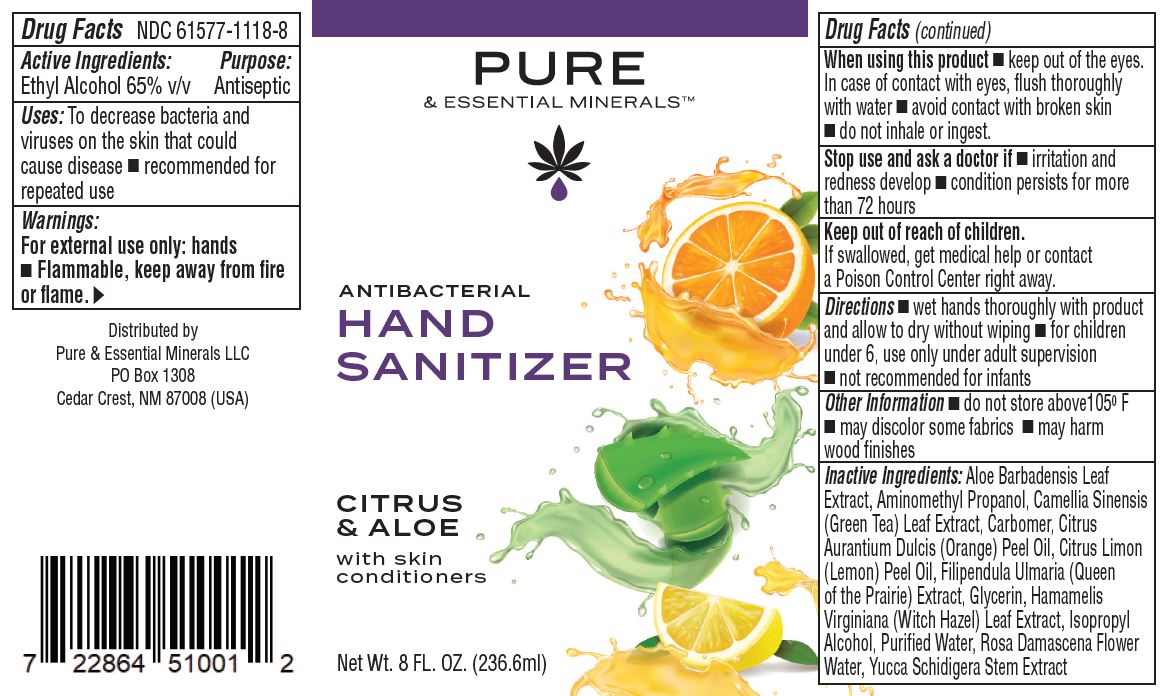 DRUG LABEL: PURE ESSENTIAL MINERALS ANTIBACTERIAL HAND SANITIZER
NDC: 61577-1118 | Form: GEL
Manufacturer: SOMBRA COSMETICS
Category: otc | Type: HUMAN OTC DRUG LABEL
Date: 20200716

ACTIVE INGREDIENTS: ALCOHOL 65 mL/100 mL
INACTIVE INGREDIENTS: ALOE VERA LEAF; AMINOMETHYLPROPANOL; CAMELLIA SINENSIS FLOWER; CARBOMER HOMOPOLYMER TYPE C; ORANGE PEEL; CITRUS LIMON FRUIT OIL; FILIPENDULA ULMARIA WHOLE; GLYCERIN; WITCH HAZEL; ISOPROPYL ALCOHOL; WATER; ROSA DAMASCENA FLOWER; YUCCA SCHIDIGERA STEM

PURE & ESSENTIAL MINERALS ANTIBACTERIAL HAND SANITIZER

Active Ingredient

Ethyl Alcohol 65%

Purpose

Antiseptic

Uses

To decrease bacteria and viruses on the skin that could cause disease

Warnings

Flammable. Keep away from fire or flame. For external use only: hands.

Do not use

When using this product, do not use in or near the eyes. In case of contact, rinse eyes thoroughly with water.

When using this product

Keept out of the eyes. In case of contact with eyes, flush shoroughly with water. Avoid contact with broke skin. Do not inhale or ingest.

Stop use and ask a doctor if irritation or rash appears and lasts. Condition persists for more than 72 hours.

Keep out of reach of children

If swallowed, get medical help or contact a Poison Control Center right away.

Directions

Wet hands thoroughly with product and allow to dry without wiping. For children under 6, use only under adult supervision. Not recommended for infants.

Other Information

Do not store above 105F. May discolor some fabrics. May harm wood finishes.

Inactive ingredients

Aloe Barbadensis Leaf Extract, Aminomethyl Propanol, Camellia Sinensis (Green Tea) Leaf Extract, Carbomer, Citrus Aurantium Dulcis (Orange) Peel
Oil, Citrus Limon (Lemon) Peel Oil, Filipendula Ulmaria, (Queen of the Prairie) Extract, Glycerin, Hamamelis Virginiana (Witch Hazel) Leaf Extract, Isopropyl Alcohol, Purified Water, Rosa Damascena Flower Water, Yucca Schidigera Stem Extract